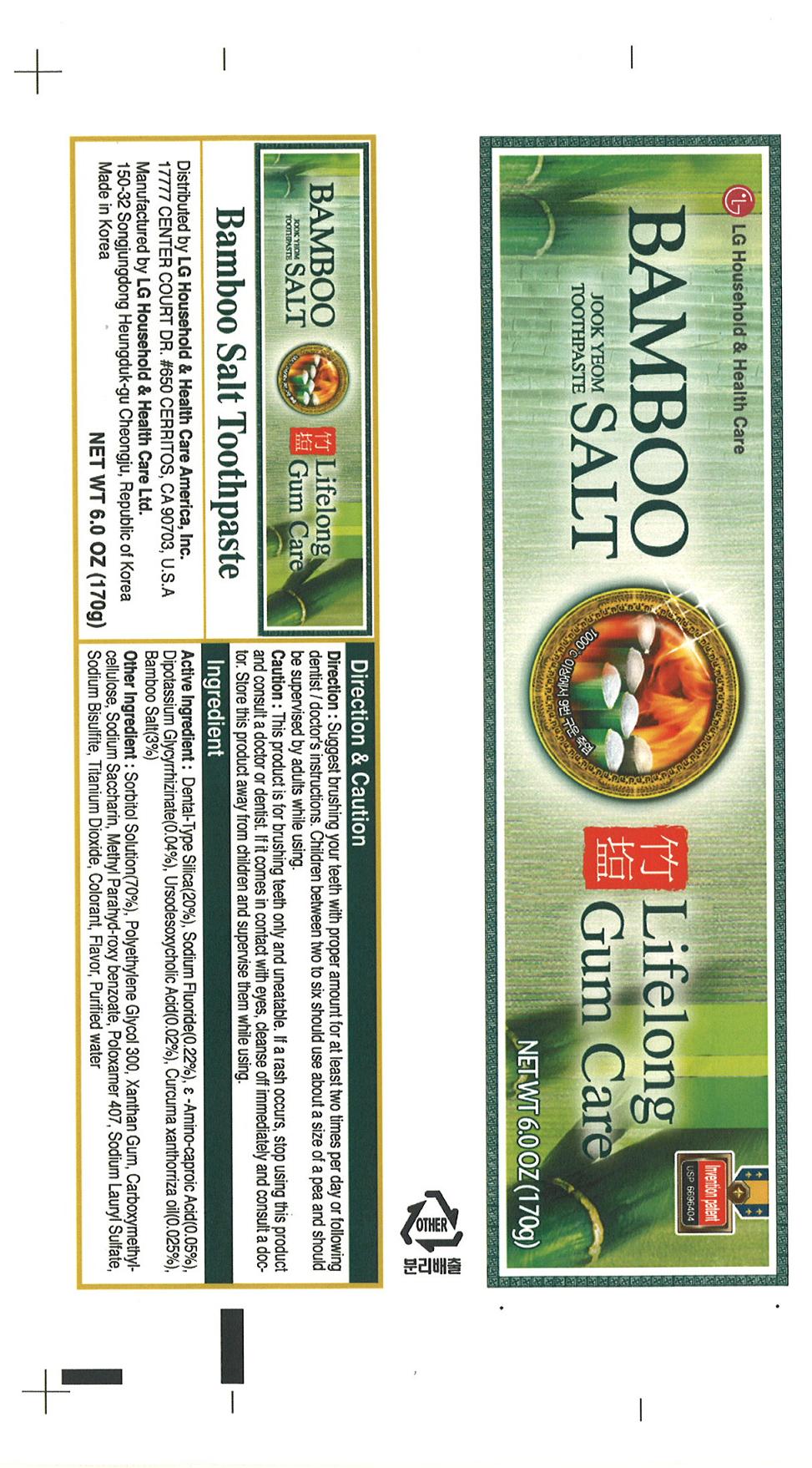 DRUG LABEL: BAMBOO SALT  Eunganggo Jook Yeom Toothpaste
NDC: 53208-459 | Form: PASTE
Manufacturer: LG Household and Healthcare, Inc.
Category: otc | Type: HUMAN OTC DRUG LABEL
Date: 20100621

ACTIVE INGREDIENTS: SILICON DIOXIDE   20 g/100 g; SODIUM FLUORIDE 0.22 g/100 g; AMINOCAPROIC ACID 0.05 g/100 g; GLYCYRRHIZINATE DIPOTASSIUM 0.04 g/100 g; URSODIOL 0.02 g/100 g; Curcuma xanthorrhiza oil 0.025 g/100 g; SEA SALT  3 g/100 g
INACTIVE INGREDIENTS: SORBITOL; Polyethylene Glycol 300; XANTHAN GUM; Poloxamer 407; Sodium Lauryl Sulfate; Sodium Bisulfite; Titanium Dioxide; WATER; Peppermint; FD&C BLUE NO. 1; D&C YELLOW NO. 10; METHYLPARABEN; SACCHARIN SODIUM

Drug Facts

ACTIVE INGREDIENT

SILICON DIOXIDE 20 %

SODIUM FLUORIDE 0.22 %

AMINOCAPROIC ACID 0.05 %

GLYCYRRHIZINATE DIPOTASSIUM 0.04 %

URSODIOL 0.02 %

SEA SALT 3 %

DOSAGE AND ADMINISTRATION

Direction: Suggested brushing your teeth with proper amount for at least two times per day or following dentist / doctor's instruction.

Children between two to six should use about two to six should use about a size of a pea and should be supervised by adults while using.

WARNINGS AND PRECAUTIONS

This product is for brushing teeth only and uneatable. If a rash occurs, stop using this product and consult a doctor or dentist.

If it comes in contact with eyes, cleanse off immediately and consult a doctor. Store this product away from children and supervise them while using.

PACKAGE LABEL

BAMBOO SALT
Eunganggo Toothpaste